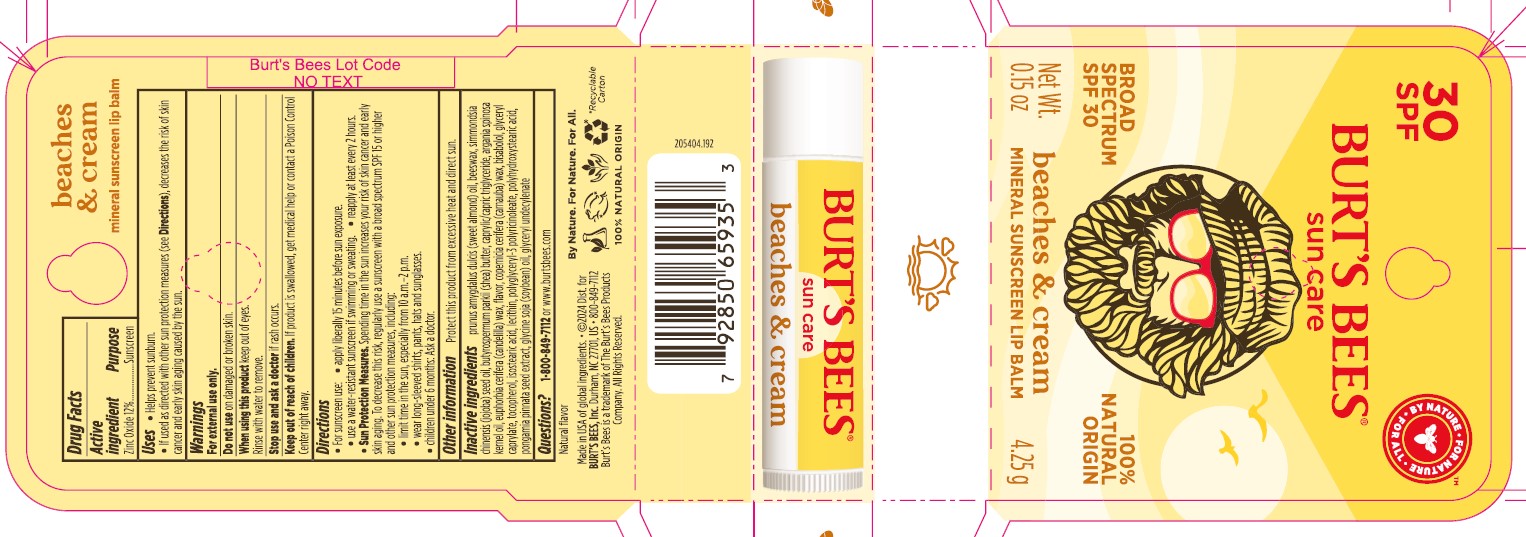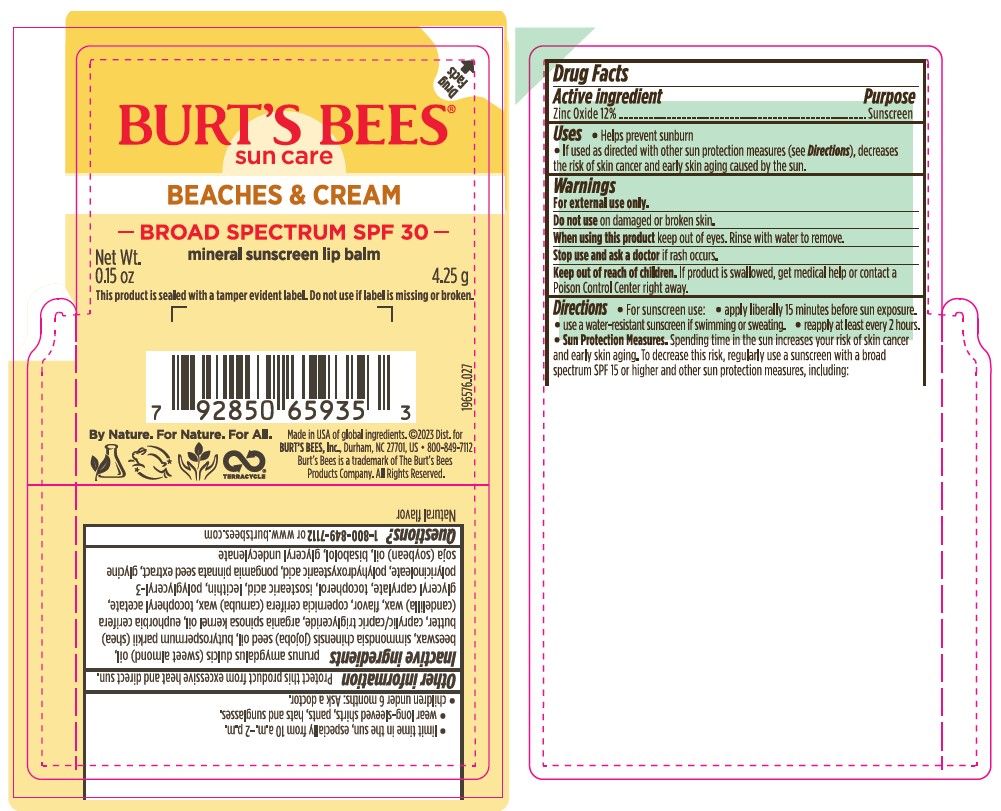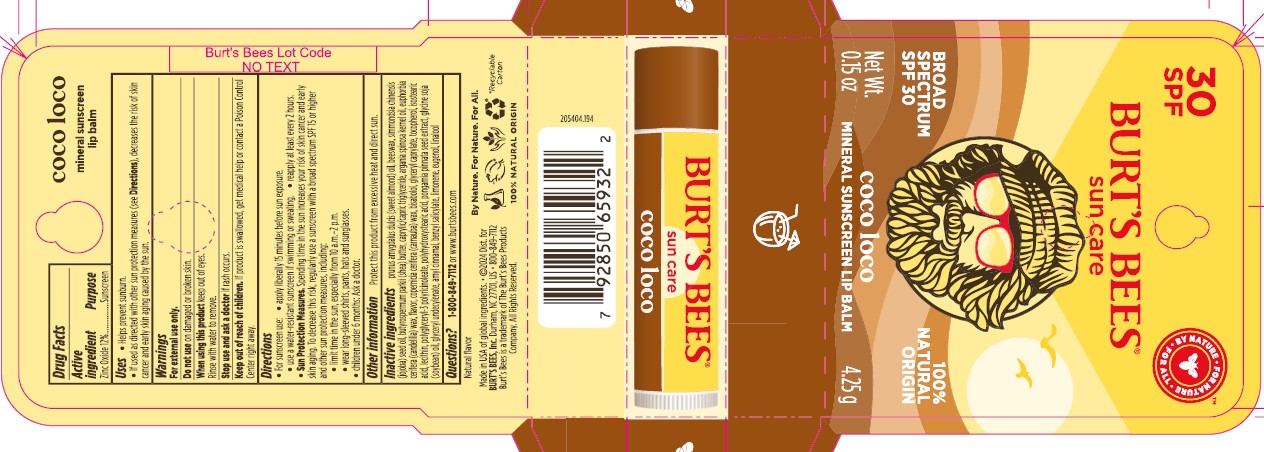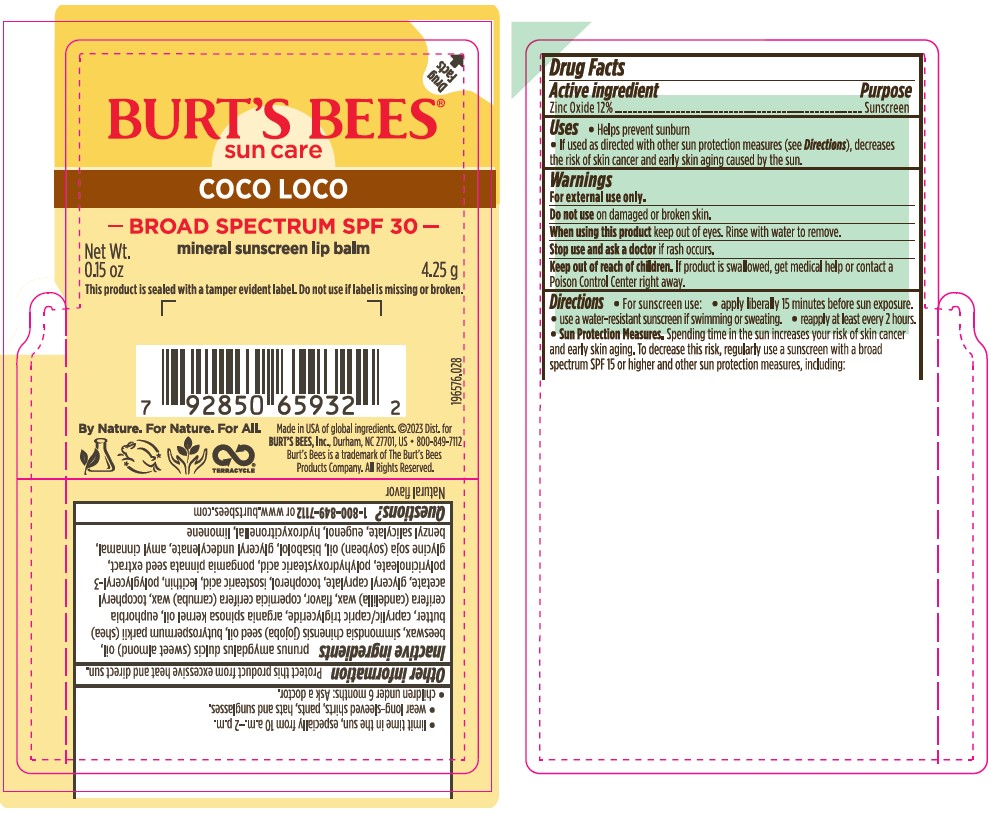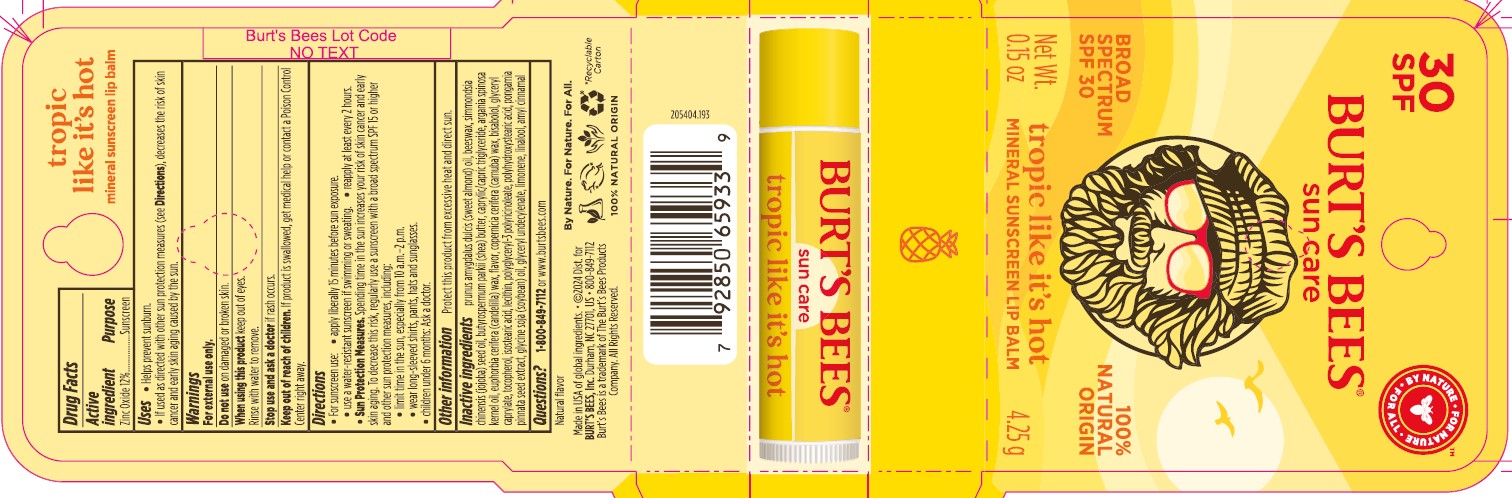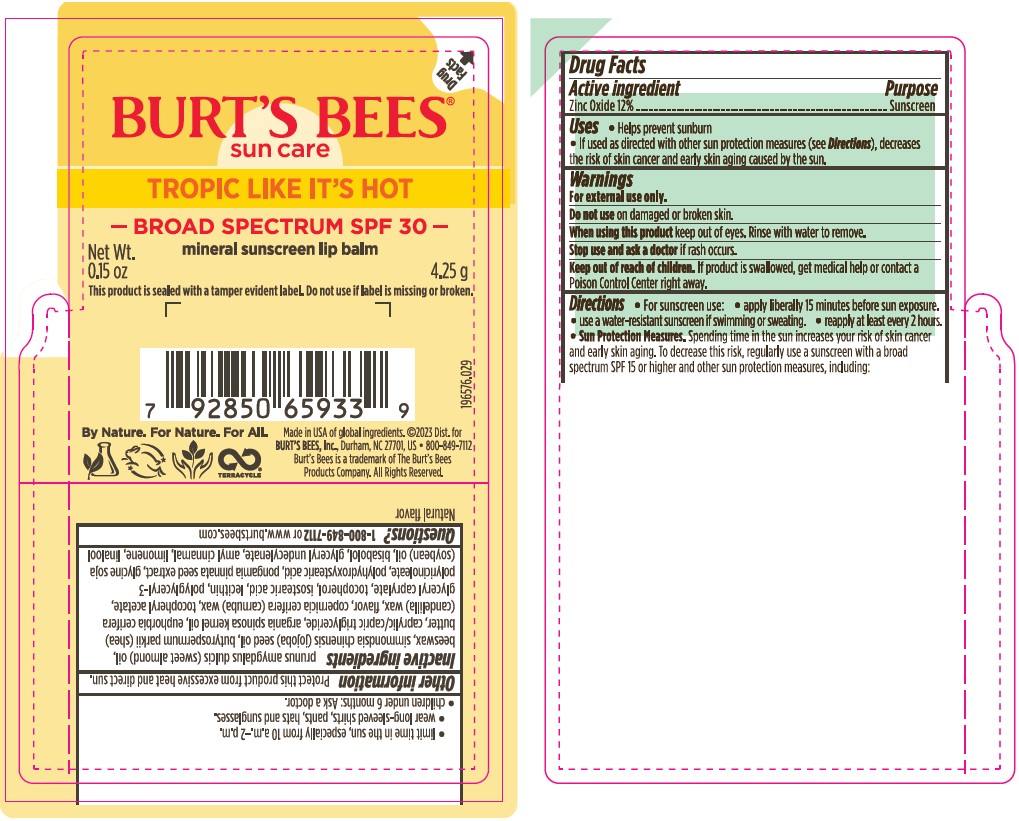 DRUG LABEL: Burts Bees SPF 30 Untinted Lip Balm Beaches and Cream
NDC: 51514-0369 | Form: STICK
Manufacturer: Autumn Harp
Category: otc | Type: HUMAN OTC DRUG LABEL
Date: 20240613

ACTIVE INGREDIENTS: ZINC OXIDE 11.99 g/100 g
INACTIVE INGREDIENTS: ALMOND OIL; CANDELILLA WAX; ISOSTEARIC ACID; CASTOR OIL; WHITE WAX; ARGAN OIL; SOYBEAN OIL; CARNAUBA WAX; POLYGLYCERYL-3 RICINOLEATE; SHEA BUTTER; .ALPHA.-TOCOPHEROL ACETATE, DL-; PONGAMIA PINNATA SEED; GLYCERYL 1-UNDECYLENATE; JOJOBA OIL; FRAGRANCE 13576; GLYCERYL CAPRYLATE; .ALPHA.-BISABOLOL, (+/-)-; MEDIUM-CHAIN TRIGLYCERIDES; .ALPHA.-TOCOPHEROL, DL-; POLYHYDROXYSTEARIC ACID (2300 MW); LECITHIN, SUNFLOWER

Burts Bees SPF 30 Untinted Lip Balms

ACTIVE INGREDIENT

Zinc Oxide 12% - Sunscreen

PURPOSE

Helps prevent sunburn if used as directed with other sun protection measures (see Directions), decreases the risk of skin cancer and early skin aging caused by the sun.

WARNINGS

For external use only

Do not use on damaged or broken skin.

When using this product keep out of eyes. Rinse with water to remove.

Stop use and ask a doctor if rash occurs.

Keep out of reach of children. If product is swallowed, get medical help or contact a Poison Control Center right away.

DOSAGE AND ADMINISTRATION

For sunscreen use:

- Apply liberally 15 minutes before sun exposure.

- Use a water-resistant sunscreen if swimming or sweating.

- Reapply at least every 2 hours.

Sun Protection Measures. Spending time in the sun increases your risk of skin cancer and early skin aging. To decrease this risk, regularly use a sunscreen with a broad spectrum SPF 15 or higher and other sun protection measures, including:

- limit time in the sun, especially from 10 a.m.-2 p.m.

- wear long-sleeved shirts, pants, hats and sunglasses.

- children under 6 months: Ask a doctor.

OTHER SAFETY INFORMATION

Protect this product from excessive heat and direct sun.

INACTIVE INGREDIENT

Beaches and Cream - Inactive Ingredients: Prunus Amygdalus Dulcis (Sweet Almond) Oil, Beeswax, Simmondsia Chinensis (Jojoba) Seed Oil, Butyrospermum Parkii (Shea) Butter, Caprylic/Capric Triglyceride, Argania Spinosa Kernel Oil, Euphorbia Cerifera (Candelilla) Wax, Ricinus Communis (Castor) Seed Oil, Copernicia Cerifera (Carnauba) Wax, Tocopheryl Acetate, Polyhydroxystearic Acid, Isostearic Acid, Lecithin, Polyglyceryl-3 Polyricinoleate, Glyceryl Caprylate, Natural Fragrance, Tocopherol, Pongamia pinnata seed extract, Bisabolol, Glycine Soja (Soybean) Oil, Glyceryl Undecylenate.

Tropic Like It's Hot - Inactive Ingredients: Prunus Amygdalus Dulcis (Sweet Almond) Oil, Beeswax, Simmondsia Chinensis (Jojoba) Seed Oil, Butyrospermum Parkii (Shea) Butter, Caprylic/Capric Triglyceride, Argania Spinosa Kernel Oil, Euphorbia Cerifera (Candelilla) Wax, Copernicia Cerifera (Carnauba) Wax, Tocopheryl Acetate, Polyhydroxystearic Acid, Natural Fragrance, Isostearic Acid, Lecithin, Polyglyceryl-3 Polyricinoleate, Glyceryl Caprylate, Tocopherol, Pongamia pinnata seed extract, Bisabolol, Glycine Soja (Soybean) Oil, Orange Oil Terpenes, Limonene, Linalool, Glyceryl Undecylenate, Amyl Cinnamal.

Coco Loco - Inactive Ingredients: Prunus Amygdalus Dulcis (Sweet Almond) Oil, Beeswax, Simmondsia Chinensis (Jojoba) Seed Oil, Butyrospermum Parkii (Shea) Butter, Caprylic/Capric Triglyceride, Argania Spinosa Kernel Oil, Euphorbia Cerifera (Candelilla) Wax, Copernicia Cerifera (Carnauba) Wax, Tocopheryl Acetate, Polyhydroxystearic Acid, Isostearic Acid, Lecithin, Polyglyceryl-3 Polyricinoleate, Glyceryl Caprylate, Tocopherol, Citrus Aurantium Dulcis (Orange) Peel Oil, Eugenia Caryophyllus (Clove) Bud Oil, Lavandula Angustifolia (Lavender) Oil, Ricinus Communis (Castor) Seed Oil, Curcuma Longa (Turmeric) Root Oil, Myristica Fragrans (Nutmeg) Kernel Oil, Natural Fragrance, Pongamia pinnata seed extract, Bisabolol, Glycine Soja (Soybean) Oil, Limonene, Glyceryl Undecylenate, Amyl Cinnamal, Benzyl Salicylate, Hydroxycitronellal, Eugenol, Linalool.

QUESTIONS

1-800-849-7112 or www.burtsbees.com

Keep out of reach of children. If product is swallowed, get medical help or contact a Poison Control Center right away

INDICATIONS AND USAGE

Helps prevent sunburn

If used as directed with other sun protection measures (see Directions), decreases the risk of skin cancer and early skin aging caused by the sun.